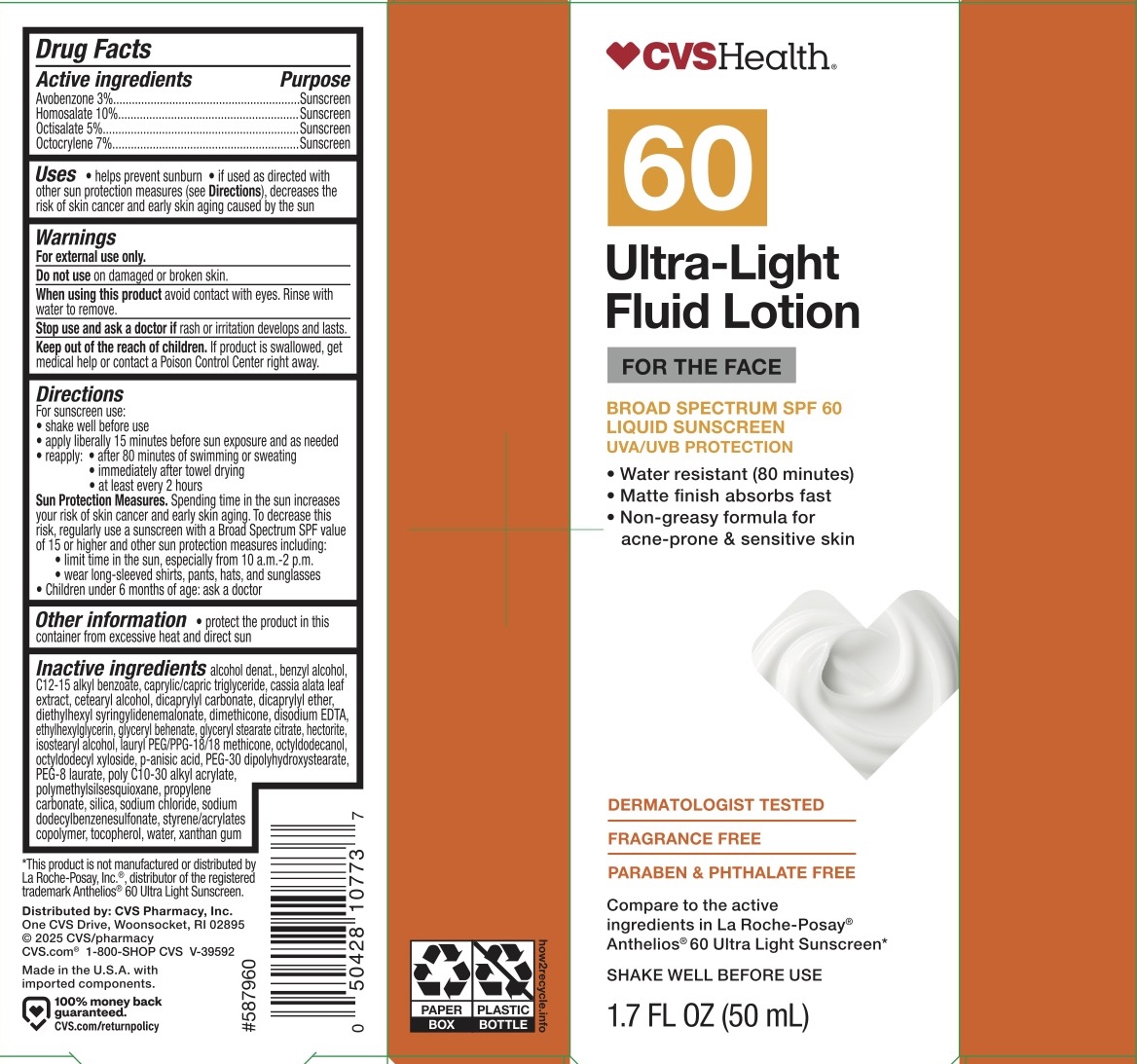 DRUG LABEL: CVS SPF 60 Face Sunscreen
NDC: 51316-922 | Form: LIQUID
Manufacturer: CVS
Category: otc | Type: HUMAN OTC DRUG LABEL
Date: 20250921

ACTIVE INGREDIENTS: OCTISALATE 5 g/100 mL; HOMOSALATE 10 g/100 mL; OCTOCRYLENE 7 g/100 mL; AVOBENZONE 3 g/100 mL
INACTIVE INGREDIENTS: DICAPRYLYL CARBONATE; CETEARYL ALCOHOL; PROPYLENE CARBONATE; P-ANISIC ACID; DIETHYLHEXYL SYRINGYLIDENEMALONATE; OCTYLDODECYL XYLOSIDE; DIMETHICONE 200; ISOSTEARYL ALCOHOL; SODIUM CHLORIDE; DIDECYL ETHER; GLYCERYL STEARATE CITRATE; BEHENYL ACRYLATE POLYMER; STYRENE/ACRYLAMIDE COPOLYMER (500000 MW); XANTHAN GUM; PEG-30 DIPOLYHYDROXYSTEARATE; OCTYLDODECANOL; SENNA ALATA LEAF; LAURYL PEG/PPG-18/18 METHICONE; SODIUM DODECYLBENZENESULFONATE; PEG-8 LAURATE; SILICA; TOCOPHEROL; WATER; ETHYLHEXYLGLYCERIN; ALCOHOL; BENZYL ALCOHOL; C12-15 ALKYL BENZOATE; CAPRYLIC/CAPRIC TRIGLYCERIDE; EDETATE DISODIUM; GLYCERYL BEHENATE/EICOSADIOATE; HECTORITE; POLYMETHYLSILSESQUIOXANE (11 MICRONS)

CVS SPF 60 Face

ACTIVE INGREDIENT

Avobenzone 3%, Homosalate 10%, Octisalate 5%, Octocrylene 7%

PURPOSE

Sunscreen

INDICATIONS AND USAGE

Helps prevent sunburn. If used as directed with other sun protection measures (see Directions), decreases the risk of skin cancer and early skin aging caused by the sun.

WARNINGS

For external use only.

Do not use on damaged or broken skin.

When using this product avoid contact with eyes. Rinse with water to remove.

Stop use and ask a doctor if rash or irritation develops and lasts.

KEEP OUT OF REACH OF CHILDREN

If product is swallowed, get medical help or contact a Poison Control Center right away.

DOSAGE AND ADMINISTRATION

For sunscreen use: shake well before use, apply liberally 15 minutes before sun exposure and as needed, reapply: after 80 minutes of swimming or sweating, immediately after towel drying, at least every 2 hours.

Sun Protection Measures. Spending time in the sun increases your risk of skin cancer and early skin aging. To decrease this risk, regularly use a sunscreen with a Broad Spectrum SPF value of 15 or higher and other sun protection measures including: limit time in the sun, especially from 10 am - 2 pm, wear long-sleeved shirts, pants, hats, and sunglasses.

Children under 6 months of age: ask a doctor.

INACTIVE INGREDIENT

Alcohol denat., benzyl alcohol, C12-15 alkyl benzoate, caprylic/capric triglyceride, cassia alata leaf extract, cetearyl alcohol, dicaprylyl carbonate, dicaprylyl ether, diethylhexyl syringylidenemalonate, dimethicone, disodium EDTA, ethylhexylglycerin, glyceryl behenate, glyceryl stearate citrate, hectorite, isostearyl alcohol, lauryl PEG/PPG-18/18 methicone, octyldodecanol, octyldodecyl xyloside, p=anisic acid, PEG-30 dipolyhydroxystearate, PEG-8 laurate, poly C10-30 alkyl acrylate, polymethylsilsesquioxane, proplyelene carbonate, silica, sodium chloride, sodium dodecylbenezenesulfonate, strene/acrylates copolymer, tocopherol, water, xanthan gum.